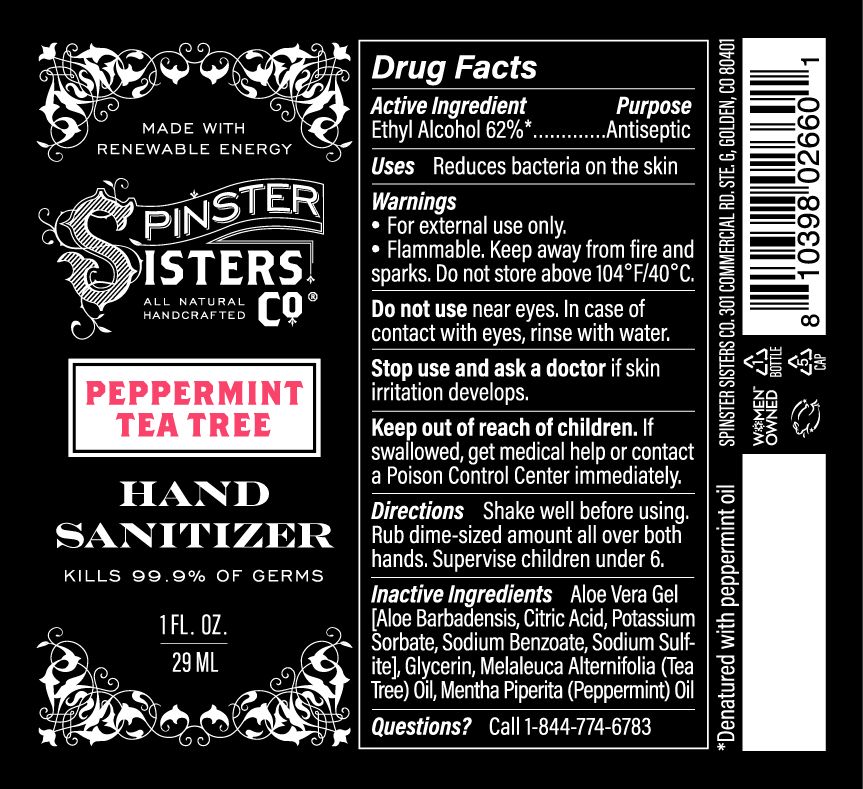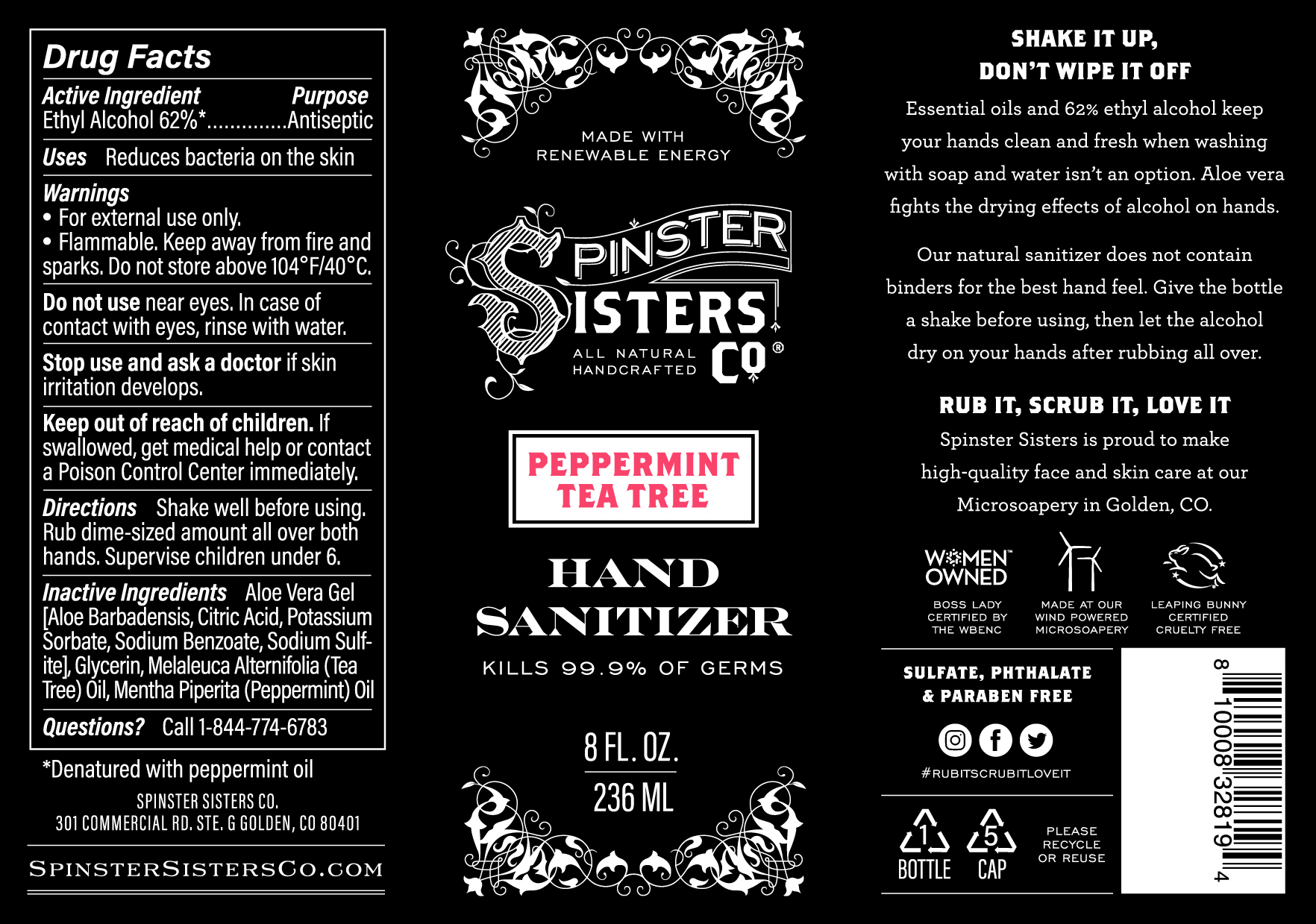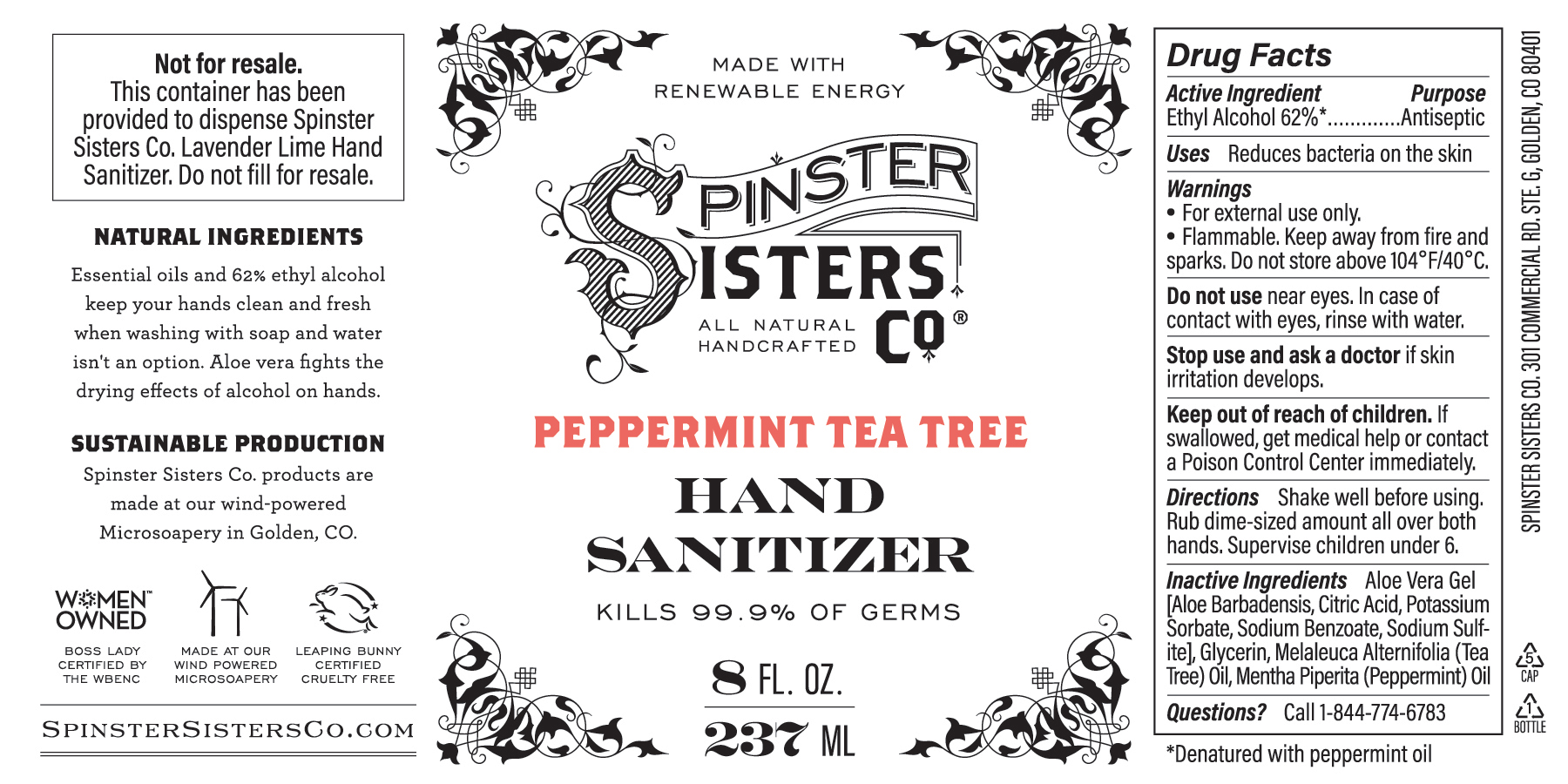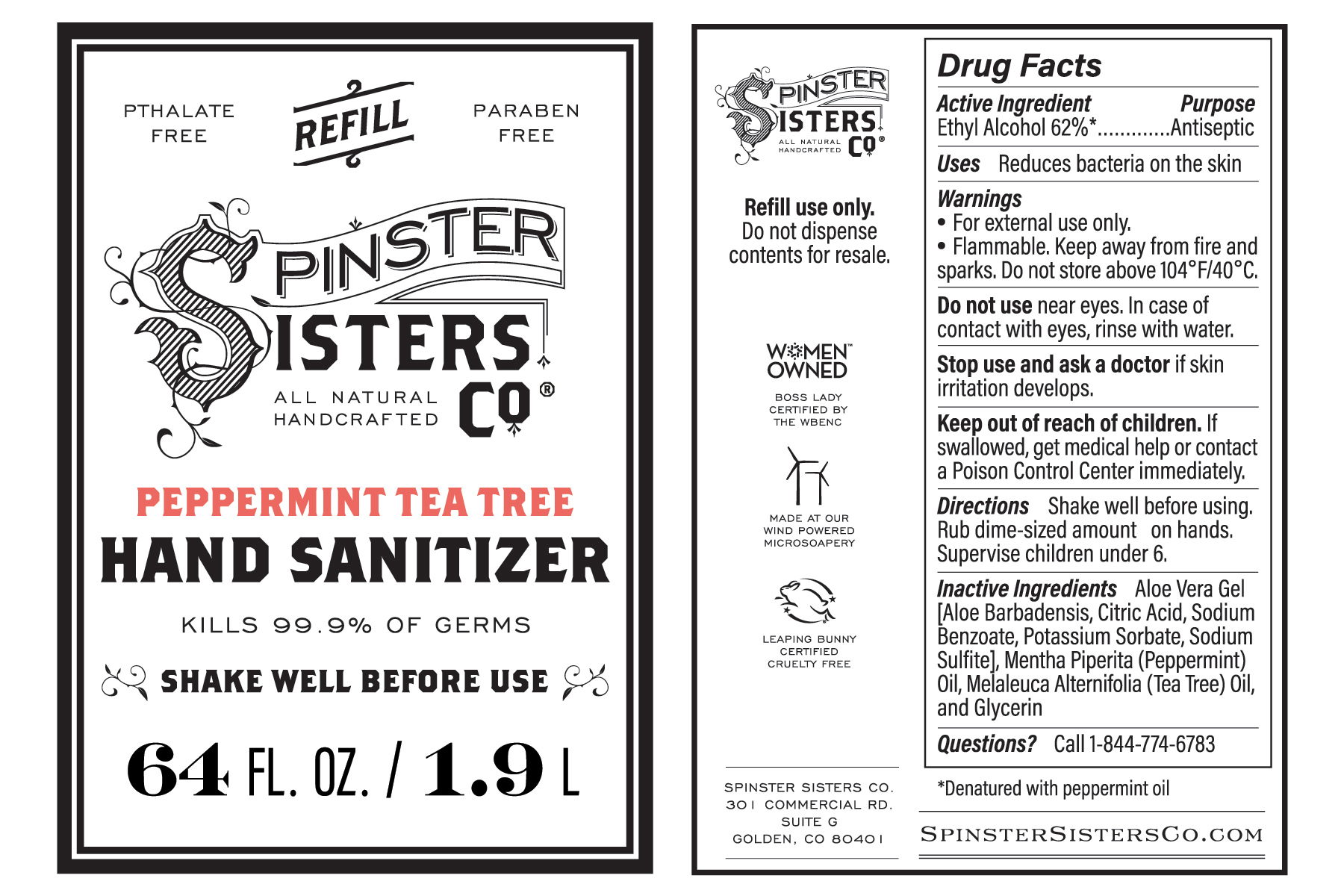 DRUG LABEL: Hand Sanitizer
NDC: 73711-103 | Form: LIQUID
Manufacturer: Spinster Sisters, Inc.
Category: otc | Type: HUMAN OTC DRUG LABEL
Date: 20211026

ACTIVE INGREDIENTS: ALCOHOL 62 mL/100 mL
INACTIVE INGREDIENTS: ALOE VERA LEAF; CITRIC ACID MONOHYDRATE; SODIUM BENZOATE; SODIUM SULFITE; POTASSIUM SORBATE; PEPPERMINT OIL; TEA TREE OIL; GLYCERIN

Hand Sanitizer Peppermint Tea Tree

Active Ingredient

Ethyl Alcohol 62%

Purpose

Antiseptic

Uses

Reduces bacteria on the skin

Warnings

- For external use only.
- Flammable. Keep away from fire and sparks. Do not store above 104°F/40°C.

Do not use

near eyes. In case of contact with eyes, rinse with water.

Stop use and ask a doctor

if skin irritation develops.

Keep out of reach of children.

If swallowed, get medical help or contact a Poison Control Center immediately.

Directions

Shake well before using. Rub dime-sized amount all over both hands. Supervise children under 6.

Directions

New version effective 4/2020: Shake well before using. Rub dime-sized amount all over both hands. Supervise children under 6.

Previous version: Rub dime-sized amount on hands. Supervise children under 6.

Inactive Ingredients

Aloe Vera Gel [Aloe Barbadensis, Citric Acid, Sodium Benzoate, Potassium Sorbate, Sodium Sulfite], Mentha Piperita (Peppermint) Oil, Melaleuca Alternifolia (Tea Tree) Oil, and Glycerin

Questions?

Call 1-844-774-6783